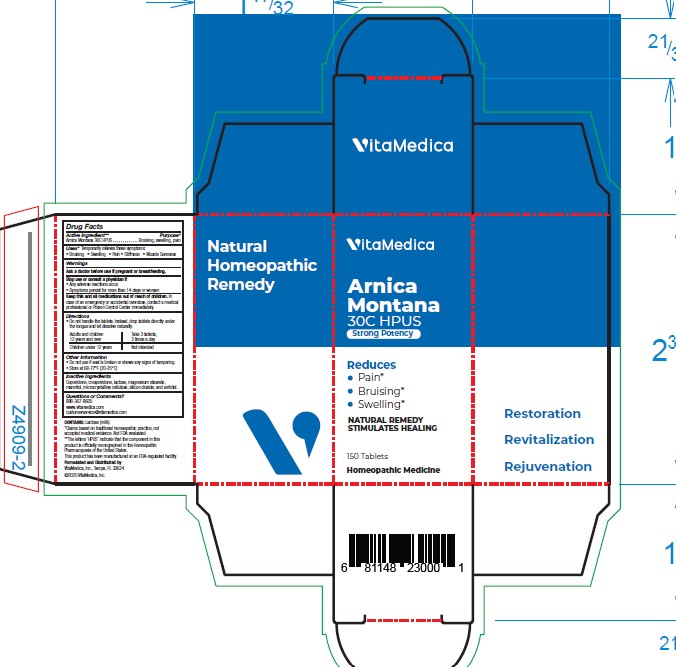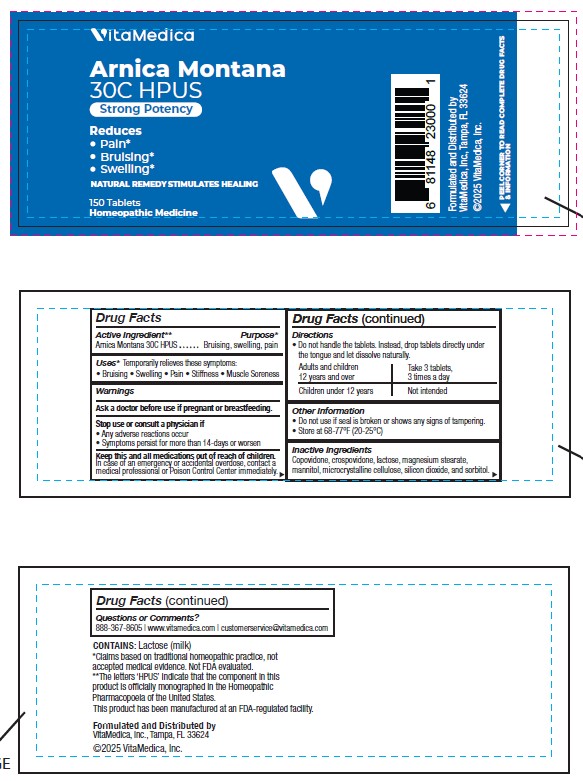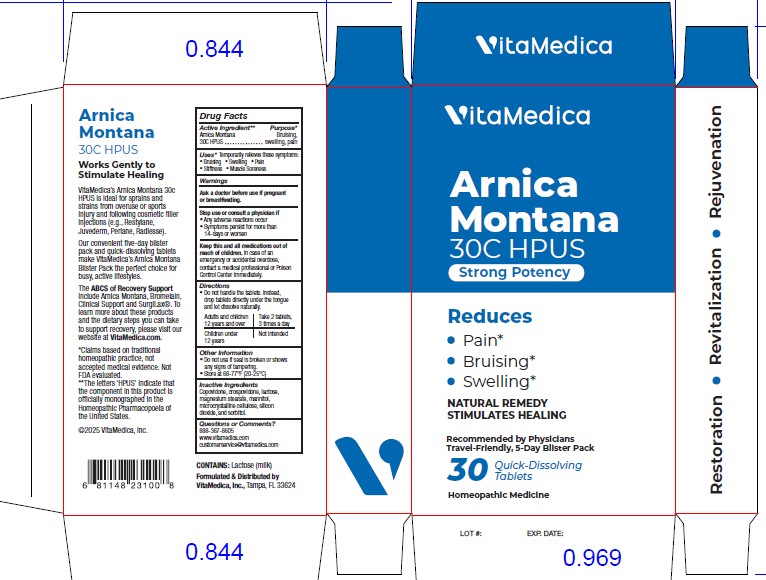 DRUG LABEL: Arnica Montana
NDC: 80004-300 | Form: TABLET
Manufacturer: VITAMEDICA, INC.
Category: homeopathic | Type: HUMAN OTC DRUG LABEL
Date: 20250828

ACTIVE INGREDIENTS: ARNICA MONTANA WHOLE 30 [hp_C]/1 1
INACTIVE INGREDIENTS: COPOVIDONE K25-31; CROSPOVIDONE; LACTOSE MONOHYDRATE; MAGNESIUM STEARATE; MANNITOL; MICROCRYSTALLINE CELLULOSE; SILICON DIOXIDE; SORBITOL

Arnica Montana 30C HPUS

ACTIVE INGREDIENT:

Arnica Montana 30C HPUS.**

**The letters 'HPUS' indicate that the component in this product is officially monographed in the Homeopathic Pharmacopoeia of the United States. This product has been manufactured at an FDA-regulated facility.

PURPOSE:

Arnica Montana - Bruising, swelling, pain*

*Claims based on traditional homeopathic practice, not accepted medical evidence. Not FDA evaluated.

USES:

*Temporarily relieves these symptoms:

• Bruising • Swelling • Pain • Stiff • Muscle Soreness

*Claims based on traditional homeopathic practice, not accepted medical evidence. Not FDA evaluated.

WARNINGS:

Ask a doctor before use if pregnant or breastfeeding.

Stop use or consult a physician if

• Any adverse reactions occur

• Symptoms persist for more than 14-days or worsen

Discontinue use if any adverse reactions occur.

Keep this and all medications out of reach of children.

In case of an emergency or accidental overdose, contact a medical professional or Poison Control immediately.

KEEP OUT OF REACH OF CHILDREN:

In case of an emergency or accidental overdose, contact a medical professional or Poison Control immediately.

DIRECTIONS:

• Do not handle the tablets. Instead, drop tablets directly under the tongue and let dissolve naturally.

Adults and children 12 years and over - Take 3 tablets, 3 times a day

Children under 12 years - Not intended

Other Information

• Do not use if seal is broken or shows any signs of tampering.

• Store at 68-77°F (20-25°C)

INACTIVE INGREDIENTS:

Copovidone, Crospovidone, Lactose, Magnesium Stearate, Mannitol, Microcrystalline Cellulose, Silicon Dioxide, and Sorbitol.

CONTAINS

Lactose (milk)

QUESTIONS:

Formulated and Distributed by

VitaMedica, Inc.

Tampa, FL 33764

©2024 VitaMedica, Inc.

888-367-8605

www.vitamedica.com

customerservice@vitamedica.com

PACKAGE DISPLAY LABEL

VitaMedica

Arnica Montana

30C HPUS•

Natural remedy Stimulates Healing*

Naturally Reduces

•Bruising*

•Muscle soreness *

•Muscle stiffness *

150 Tablets

Homeopathic Medicine

NDC 80004-300-10

150 Count Bottle

1 Bottle Per carton

VitaMedica

Arnica Montana

30C HPUS•

Natural remedy Stimulates Healing*

Naturally Reduces

•Bruising*

•Muscle soreness *

•Muscle stiffness *

150 Tablets

Homeopathic Medicine

NDC 80004-300-10

30 Count Blister

1 Blister Per carton